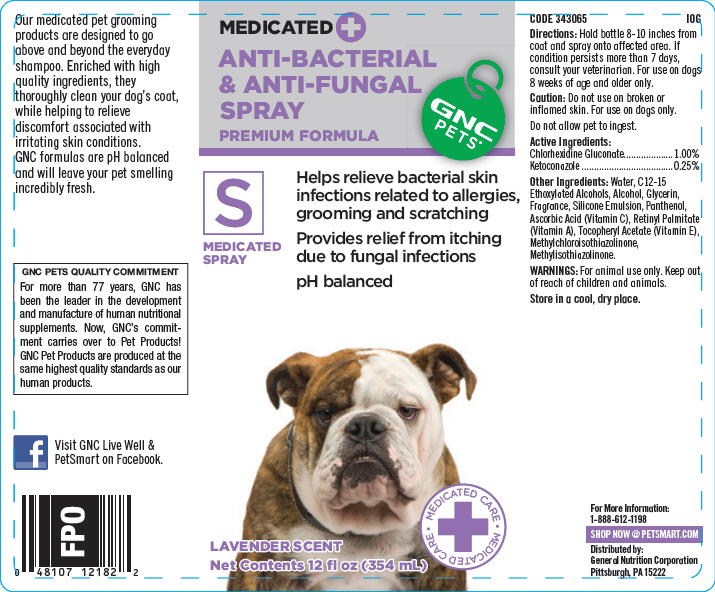 DRUG LABEL: GNC Pets Anti-Bacterial and Anti-Fungal (Premium Formula)
NDC: 43655-006 | Form: SPRAY
Manufacturer: General Nutrition Corporation
Category: animal | Type: OTC ANIMAL DRUG LABEL
Date: 20181105

ACTIVE INGREDIENTS: Chlorhexidine Gluconate 10 mg/1 mL; Ketoconazole 2.5 mg/1 mL
INACTIVE INGREDIENTS: Water; Alcohol; Glycerin; Panthenol; Ascorbic Acid; Vitamin A Palmitate; .Alpha.-Tocopherol Acetate; Methylchloroisothiazolinone; Methylisothiazolinone

GNC Pets® Anti-Bacterial & Anti-Fungal Spray (Premium Formula)

CODE 343065
IOG

INDICATIONS AND USAGE

Directions: Hold bottle 8-10 inches from coat and spray onto affected area. If condition persists more than 7 days, consult your veterinarian. For use on dogs 8 weeks of age and older only.

Caution: Do not use on broken or inflamed skin. For use on dogs only.

Do not allow pet to ingest.

Active Ingredients:
Chlorhexidine Gluconate | 1.00%
Ketoconazole | 0.25%

Other Ingredients: Water, C12-15 Ethoxylated Alcohols, Alcohol, Glycerin, Fragrance, Silicone Emulsion, Panthenol, Ascorbic Acid (Vitamin C), Retinyl Palmitate (Vitamin A), Tocopheryl Acetate (Vitamin E), Methylchloroisothiazolinone, Methylisothiazolinone.

WARNINGS: For animal use only. Keep out of reach of children and animals.

STORAGE AND HANDLING

Store in a cool, dry place.

For More Information:
1-888-612-1198

SHOP NOW @ PETSMART.COM

Distributed by:
General Nutrition Corporation
Pittsburgh, PA 15222

PRINCIPAL DISPLAY PANEL - 354 mL Bottle Label

MEDICATED +
ANTI-BACTERIAL
& ANTI-FUNGAL
SPRAY
PREMIUM FORMULA

GNC
PETS®

S
MEDICATED
SPRAY

Helps relieve bacterial skin
infections related to allergies,
grooming and scratching

Provides relief from itching
due to fungal infections

pH balanced

• MEDICATED CARE
+
• MEDICATED CARE

LAVENDER SCENT
Net Contents 12 fl oz (354 mL)